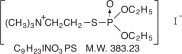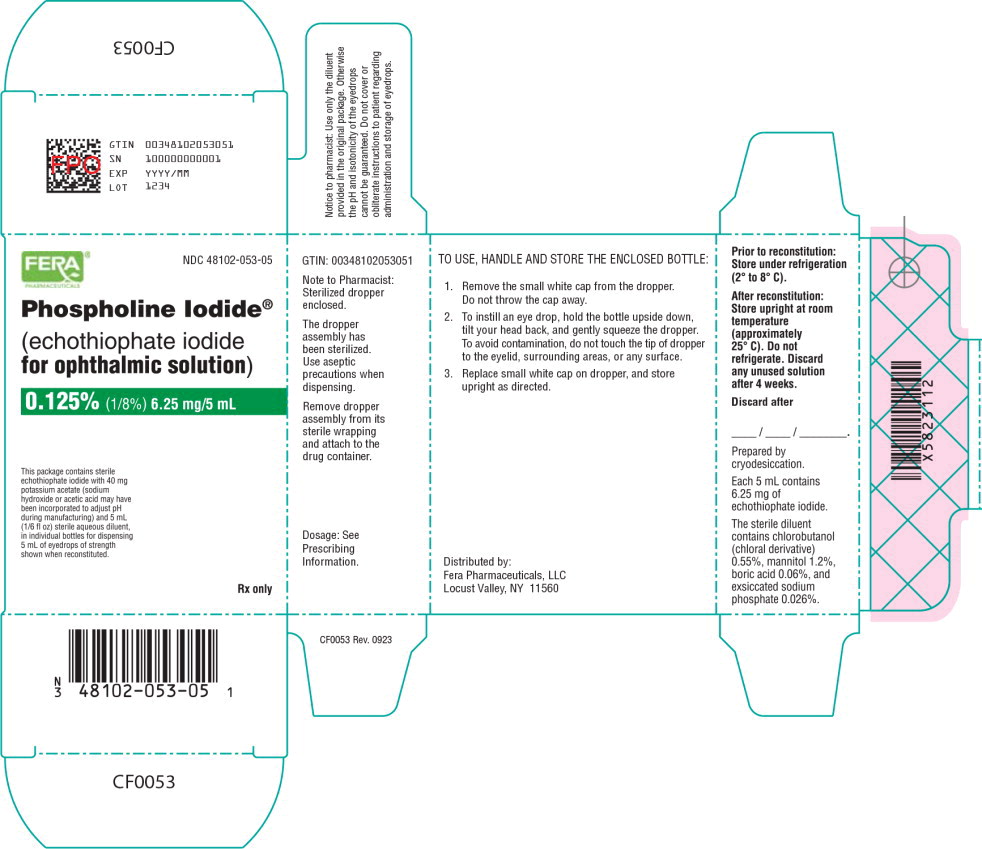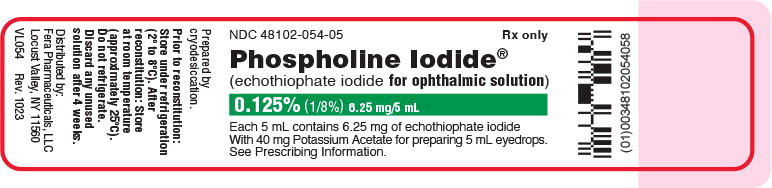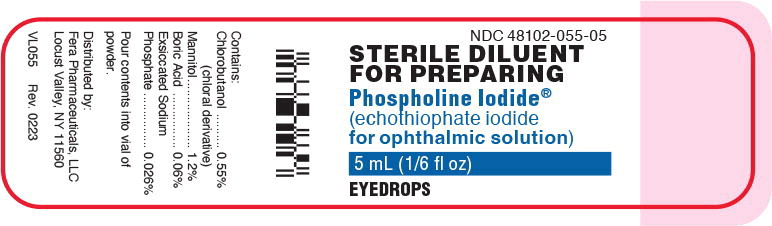 DRUG LABEL: Phospholine Iodide
NDC: 48102-053 | Form: KIT | Route: OPHTHALMIC
Manufacturer: Fera Pharmaceuticals, LLC
Category: prescription | Type: HUMAN PRESCRIPTION DRUG LABEL
Date: 20250707

ACTIVE INGREDIENTS: echothiophate iodide 6.25 mg/5 mL
INACTIVE INGREDIENTS: potassium acetate 40 mg/5 mL; chlorobutanol 27.5 mg/5 mL; mannitol 60 mg/5 mL; boric acid 3 mg/5 mL; sodium phosphate 1.3 mg/5 mL; water 5 mL/5 mL

Phospholine Iodide®
(echothiophate iodide for
ophthalmic solution)

Rx only

DESCRIPTION

Chemical name: (2-mercaptoethyl) trimethylammonium iodide O,O-diethyl phosphorothioate

Structural formula

Echothiophate iodide for ophthalmic solution occurs as a white, crystalline, water-soluble, hygroscopic solid having a slight mercaptan-like odor. When freeze-dried in the presence of potassium acetate, the mixture appears as a white amorphous deposit on the walls of the bottle.

Each package contains materials for dispensing 5 mL of eyedrops: (1) bottle containing sterile echothiophate iodide for ophthalmic solution 6.25 mg (0.125%) with 40 mg potassium acetate. Sodium hydroxide or acetic acid may have been incorporated to adjust pH during manufacturing; (2) a 5 mL bottle of sterile diluent containing chlorobutanol (chloral derivative), 0.55%; mannitol, 1.2%; boric acid, 0.06%; and sodium phosphate, 0.026%; (3) sterilized dropper.

CLINICAL PHARMACOLOGY

Echothiophate iodide for ophthalmic solution is a long-acting cholinesterase inhibitor for topical use which enhances the effect of endogenously liberated acetylcholine in iris, ciliary muscle, and other parasympathetically innervated structures of the eye. It thereby causes miosis, increase in facility of outflow of aqueous humor, fall in intraocular pressure (IOP), and potentiation of accommodation.

Echothiophate iodide for ophthalmic solution will depress both plasma and erythrocyte cholinesterase levels in most patients after a few weeks of eyedrop therapy.

INDICATIONS AND USAGE

Reduction of Elevated IOP

Echothiophate iodide for ophthalmic solution is indicated for the reduction of elevated IOP.

Accommodative Esotropia

Concomitant esotropias with a significant accommodative component.

CONTRAINDICATIONS

1. Active uveal inflammation.
2. Most cases of angle-closure glaucoma without iridectomy, due to the possibility of increasing angle block.
3. Hypersensitivity to the active or inactive ingredients.

WARNINGS

1. Succinylcholine should be administered only with great caution, if at all, prior to or during general anesthesia to patients receiving anticholinesterase medication because of possible respiratory or cardiovascular collapse.
2. Caution should be observed in treating elevated IOP with echothiophate iodide for ophthalmic solution in patients who are at the same time undergoing treatment with systemic anticholinesterase medications, because of possible adverse additive effects.

PRECAUTIONS

General

1. Digital compression of the nasolacrimal ducts for a minute or two following instillation to minimize drainage into the nasal chamber is recommended. To prevent possible skin absorption, hands should be washed following instillation.
2. Discontinue use of the medication if cardiac irregularities occur.
3. Anticholinesterase drugs should be used with caution, if at all, in patients with marked vagotonia, bronchial asthma, spastic gastrointestinal disturbances, peptic ulcer, pronounced bradycardia and hypotension, recent myocardial infarction, epilepsy, parkinsonism, and other disorders that may respond adversely to vagotonic effects.
4. Echothiophate iodide for ophthalmic solution should be used with caution, where there is a prior history of retinal detachment.
5. Temporary discontinuance of medication is necessary if salivation, urinary incontinence, diarrhea, profuse sweating, muscle weakness, or respiratory difficulties occur.
6. Patients receiving echothiophate iodide for ophthalmic solution who are exposed to carbamate- or organophosphate-type insecticides and pesticides should be warned of the additive systemic effects possible from absorption of the pesticide through the respiratory tract or skin. During periods of exposure to such pesticides, the wearing of respiratory masks, and frequent washing and clothing changes may be advisable.

Drug Interactions

Echothiophate iodide for ophthalmic solution potentiates other cholinesterase inhibitors such as succinylcholine or organophosphate and carbamate insecticides. Patients undergoing systemic anticholinesterase treatment should be warned of the possible additive effects of echothiophate iodide for ophthalmic solution.

Carcinogenesis, Mutagenesis, Impairment of Fertility

No data is available regarding carcinogenesis, mutagenesis, and impairment of fertility.

Pregnancy

Teratogenic Effects

Animal reproduction studies have not been conducted with echothiophate iodide for ophthalmic solution. It is also not known whether echothiophate iodide for ophthalmic solution can cause fetal harm when administered to a pregnant woman or can affect reproduction capacity. Echothiophate iodide for ophthalmic solution should be given to a pregnant woman only if clearly needed.

Nursing Mothers

Because of the potential for serious adverse reactions in nursing infants from echothiophate iodide for ophthalmic solution, a decision should be made whether to discontinue nursing or to discontinue the drug, taking into account the importance of the drug to the mother.

Pediatric Use

Safety and effectiveness in pediatric patients have been established.

Geriatric Use

No overall differences in safety or effectiveness have been observed between elderly and younger patients.

ADVERSE REACTIONS

1. Although the relationship, if any, of retinal detachment to the administration of echothiophate iodide for ophthalmic solution has not been established, retinal detachment has been reported in a few cases during the use of echothiophate iodide for ophthalmic solution in adult patients without a previous history of this disorder.
2. Stinging, burning, lacrimation, lid muscle twitching, conjunctival and ciliary redness, browache, induced myopia with visual blurring may occur.
3. Activation of latent iritis or uveitis may occur.
4. Iris cysts may form, and if treatment is continued, may enlarge and obscure vision. This occurrence is more frequent in children. The cysts usually shrink upon discontinuance of the medication or by reducing the frequency of instillation. Rarely, they may rupture or break free into the aqueous. Regular examinations are advisable when the drug is being prescribed for the treatment of accommodative esotropia.
5. Prolonged use may cause conjunctival thickening, obstruction of nasolacrimal canals.
6. Lens opacities have been reported with echothiophate iodide.
7. Paradoxical increase in IOP may follow anticholinesterase instillation. This may be alleviated by prescribing a sympathomimetic mydriatic such as phenylephrine.
8. Cardiac irregularities.

Directions for Preparing Eyedrops

1. Use aseptic technique.
2. Tear off aluminum seals and remove and discard rubber plugs from both drug and diluent containers.
3. Pour diluent into drug container.
4. Remove dropper assembly from its sterile wrapping and attach to the drug container.
5. Shake for several seconds to ensure mixing.
6. Do not cover nor obliterate instructions to patient regarding administration and storage of eyedrops.

Elevated IOP

Echothiophate iodide for ophthalmic solution one drop instilled twice a day, just before retiring and in the morning. A change in therapy is indicated if, at any time, the tension fails to remain at an acceptable level on this regimen.

Two doses a day are preferred to one in order to maintain as smooth a diurnal tension curve as possible, although a single dose per day or every other day has been used with satisfactory results. The daily dose or one of the two daily doses should always be instilled just before retiring to avoid inconvenience due to the miosis.

Technique – Technique in the administration of echothiophate iodide for ophthalmic solution may include finger pressure at the inner canthus exerted for a minute or two following instillation of the eyedrops, to potentially minimize drainage into the nose and throat. Excess solution around the eye should be removed with tissue and any medication on the hands should be rinsed off.

Accommodative Esotropia (Pediatric Use)

In Diagnosis – One drop may be instilled once a day in both eyes on retiring, for a period of two or three weeks. If the esotropia is accommodative, a favorable response will usually be noted which may begin within a few hours.

In Treatment – Echothiophate iodide for ophthalmic solution is prescribed at the lowest frequency which gives satisfactory results. After the initial period of treatment for diagnostic purposes, the schedule may be reduced to one drop every other day. The maximum usually recommended dosage is one drop once a day, although more intensive therapy has been used for short periods.

Technique – (See “DOSAGE AND ADMINISTRATION”)

Duration of Treatment — In therapy, there is no definite limit so long as the drug is well tolerated. However, if the eyedrops, with or without eyeglasses, are gradually withdrawn after about a year or two and deviation recurs, surgery should be considered. As with other miotics, tolerance may occasionally develop after prolonged use. In such cases, a rest period may restore the original activity of the drug.

HOW SUPPLIED

Each package contains sterile echothiophate iodide for ophthalmic solution, sterile diluent, and dropper for dispensing 5 mL eyedrops.

NDC 48102-053-05 ................... 6.25 mg package for 0.125%

White amorphous deposit on bottle walls. Aluminum crimp seal is green.

HANDLING AND STORAGE:

Prior to reconstitution: Store under refrigeration (2°C to 8°C).

After reconstitution: Store upright at room temperature (approximately 25°C)

(68°F to 77° F).

Do not refrigerate. Discard any unused solution after 4 weeks.

FERA®
PHARMACEUTICALS
Distributed by:
Fera Pharmaceuticals, LLC
Locust Valley, NY 11560
PF053

Rev. 0923

Principal Display Panel - 6.25 mg/5 mL Carton Label

FERA®
PHARMACEUTICALS

NDC 48102-053-05

Phospholine Iodide®

(echothiophate iodide
for ophthalmic solution)

0.125% (1/8%) 6.25 mg/5 mL

This package contains sterile
echothiophate iodide with 40 mg
potassium acetate (sodium
hydroxide or acetic acid may have
been incorporated to adjust pH
during manufacturing) and 5 mL
(1/6 fl oz) sterile aqueous diluent,
in individual bottles for dispensing
5 mL of eyedrops of strength
shown when reconstituted.

Rx only

Principal Display Panel - 6.25 mg/5 mL Bottle Label

NDC 48102-054-05

Rx only

Phospholine Iodide®

(echothiophate iodide
for ophthalmic solution)

0.125% (1/8%) 6.25 mg/5 mL

Each 5 mL contains 6.25 mg of echothiophate iodide
With 40 mg Potassium Acetate for preparing 5 mL eyedrops.

See Prescribing Information.

Principal Display Panel - 5 mL Bottle Label

NDC 48102-055-05

STERILE DILUENT
FOR PREPARING
Phospholine Iodide®

(echothiophate iodide

for ophthalmic solution)

5 mL (1/6 fl oz)

EYEDROPS